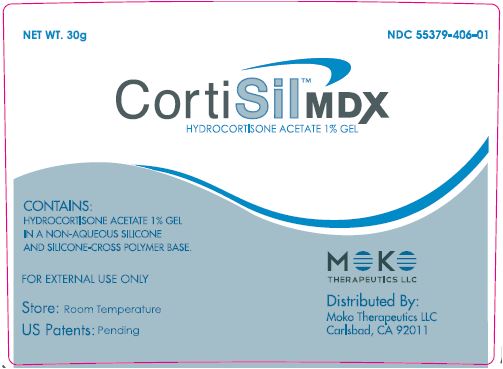 DRUG LABEL: CortiSil MDX
NDC: 55379-406 | Form: GEL
Manufacturer: BioZone Laboratories,Inc.
Category: otc | Type: HUMAN OTC DRUG LABEL
Date: 20130301

ACTIVE INGREDIENTS: HYDROCORTISONE ACETATE 1 g/100 g
INACTIVE INGREDIENTS: CYCLOMETHICONE 5; DIMETHICONE; CYCLOMETHICONE; PEG-12 GLYCERYL DIMYRISTATE; EDETATE DISODIUM

Drug Facts

Active ingredient
Hydrocortisone Acetate 1.0%

Purpose
Anti-Pruritic

Use

For the temporary relief of itching associated with minor skin irritations, inflammation and rashes.

Warnings

For external use only

Do not use

- hydrocortisone product unless you have consulted a doctor.
- on children under 2 years of age.
- on mucous membranes

When using this product

- avoid contact with the eyes.
- If irritation develops, topical corticosteroids should be discontinued and appropriate therapy instituted.

Stop use and ask a doctor if

- condition worsens
- symptoms persist for more than 7 days or clear up and occur again within a few days.

Keep out of reach of children.

If swallowed, get medical help or contact a Poison Control Center immediately.

Directions

Adults and children 2 years of age and older: Apply to the affected area not more than 3 to 4 times daily. Children under 2 year of age: consult a doctor.

Other information

Store at 15° to 30° C (59° to 86°F)

Carton: 1oz applicator pump

Inactive ingredients

Cyclopentasiloxane, Dimethicone Crosspolymer, Cyclomethicone, PEG-12 Glyceryl Dimyristate, Disodium EDTA.

Questions?

call 1-760-734-3622

PACKAGE LABEL.PRINCIPAL DISPLAY PANEL

NET WT. 30G NDC 55379-406-01

CortiSILTMMDX
HYDROCORTISONE ACETATE 1% GEL

CONTAINS:
HYDROCORTISONE ACETATE 1% GEL
IN A NON-AQUEOUS SILICONE
AND SILICONE-CROSS POLYMER BASE.

FOR EXTERNAL USE ONLY

Store: Room Temperature

US Patents: Pending

MOKO
THERAPEUTICS LLC

Distributed By:
Moko Therapeutics LLC
Carlsbad, CA 92011